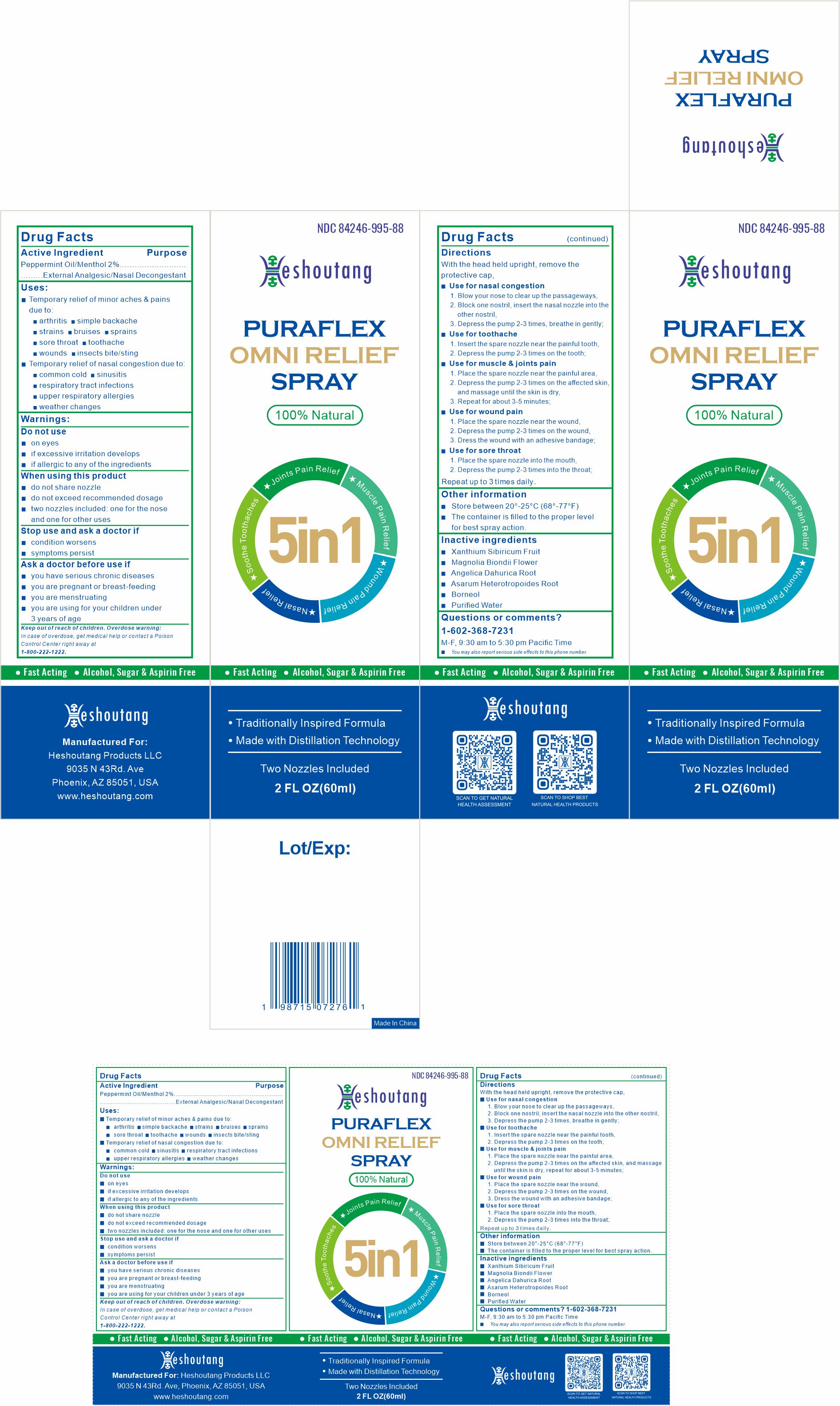 DRUG LABEL: Heshoutang PuraFlex OmniRelief
NDC: 84246-995 | Form: SPRAY
Manufacturer: Shandong Huawei Pharmaceutical Co., Ltd.
Category: otc | Type: HUMAN OTC DRUG LABEL
Date: 20240621

ACTIVE INGREDIENTS: MENTHOL 1.8 mg/10 mL
INACTIVE INGREDIENTS: ASARUM HETEROTROPOIDES ROOT; MAGNOLIA BIONDII FLOWER; WATER; BORNEOL; XANTHIUM SIBIRICUM FRUIT; ANGELICA DAHURICA ROOT

ACTIVE INGREDIENT

Peppermint Oil/Menthol 2%

PURPOSE

External Analgesic/Nasal Decongestant

USES

Temporary relief of minor aches & pains due to:-arthritis-simple backache-strains-bruises-sprains-sore throat-toothache-wounds-insects bite/sting;

Temporary relief of nasal congestion due to:-common cold-sinusitis-respiratory tract infections-upper respiratory allergies-weather changes.

WARNINGS

Do not use-on eyes-if excessive irritation develops-if allergic to any of the ingredients

WHEN USING THIS PRODUCT

do not share nozzle-do not exceed recommended dosage-two nozzles included: one for the nose and one for other uses

STOP USE AND ASK A DOCTOR IF

condition worsens-symptoms persist

ASK A DOCTOR BEFORE USE IF

you have serious chronic diseases-you are pregnant or breast-feeding-you are menstruating-you are using for your children under 3 years of age.

KEEP OUT OF REACH OF CHILDREN. OVERDOSE WARNING:

In case of overdose, get medical help or contact a Poison Control Center right away at 1-800-222-1222.

DIRECTIONS

With the head held upright, remove the protective cap,

Use for nasal congestion-1. Blow your nose to clear up the passageways,-2. Block one nostril, insert the nasal nozzle into the other nostril,-3. Depress the pump 2-3 times, breathe in gently;

Use for toothache-1. Insert the spare nozzle near the painful tooth,-2. Depress the pump 2-3 times on the tooth;

Use for muscle & joints pain-1. Place the spare nozzle near the painful area,-2. Depress the pump 2-3 times on the affected skin, and massage until the skin is dry,-3. Repeat for about 3-5 minutes;

Use for wound pain-1. Place the spare nozzle near the wound,-2. Depress the pump 2-3 times on the wound,-3. Dress the wound with an adhesive bandage;

Use for sore throat-1. Place the spare nozzle into the mouth,-2. Depress the pump 2-3 times into the throat;

Repeat up to 3 times daily.

OTHER INFORMATION

Store between 20°-25°C (68°-77°F)-The container is filled to the proper level for best spray action.

INACTIVE INGREDIENTS

Xanthium Sibiricum Fruit, Magnolia Biondii Flower, Angelica Dahurica Root, Asarum Heterotropoides Root, Borneol, Purified Water.

QUESTIONS OR COMMENTS? (602) 368-7231

M-F, 9:30 am to 5:30 pm Pacific Time - You may also report serious side effects to this phone number.

MANUFACTURED FOR HESHOUTANG PRODUCTS LLC

9035 N 43rd Ave, Phoenix, AZ 85051, USA
www.heshoutang.com

Made in China